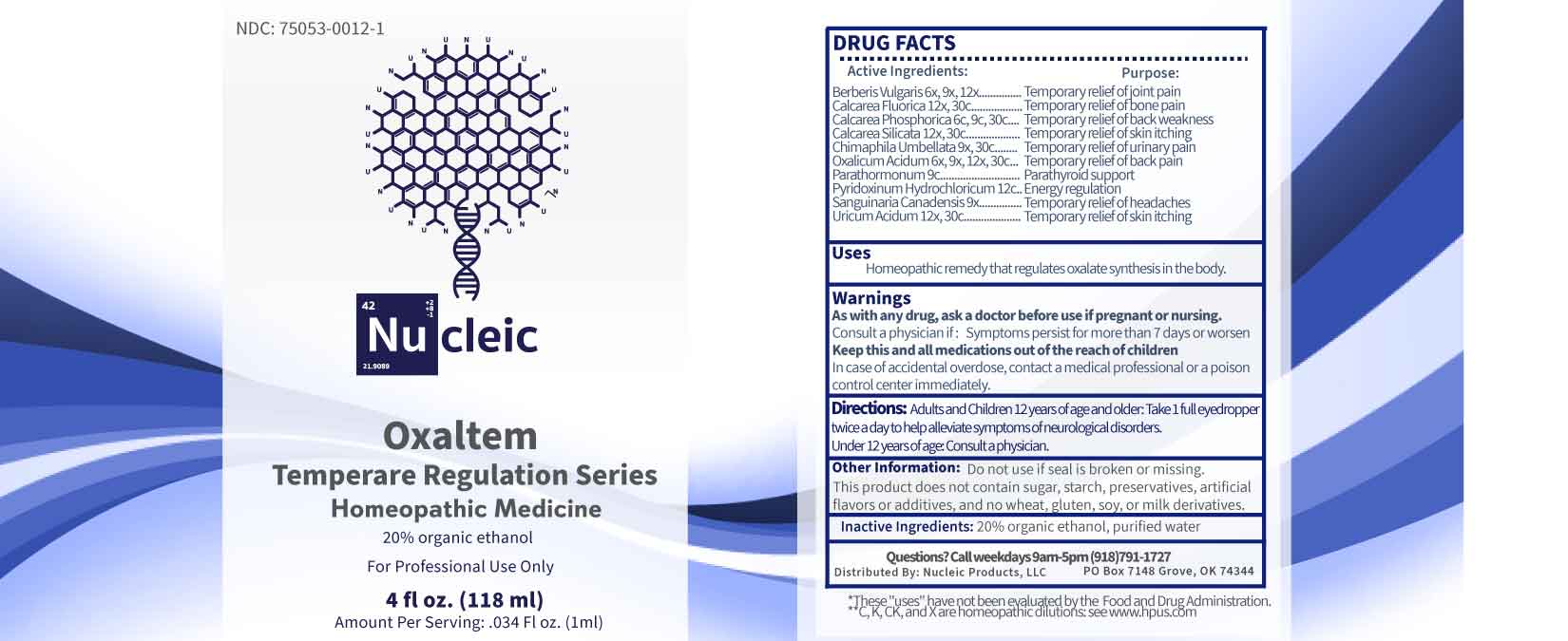 DRUG LABEL: Oxaltem
NDC: 75053-0012 | Form: LIQUID
Manufacturer: Nucleic Products, LLC
Category: homeopathic | Type: HUMAN OTC DRUG LABEL
Date: 20251124

ACTIVE INGREDIENTS: BERBERIS VULGARIS ROOT BARK 6 [hp_X]/1 mL; OXALIC ACID DIHYDRATE 6 [hp_X]/1 mL; SANGUINARIA CANADENSIS ROOT 9 [hp_X]/1 mL; CHIMAPHILA UMBELLATA WHOLE 9 [hp_X]/1 mL; CALCIUM FLUORIDE 12 [hp_X]/1 mL; CALCIUM SILICATE 12 [hp_X]/1 mL; URIC ACID 12 [hp_X]/1 mL; TRIBASIC CALCIUM PHOSPHATE 6 [hp_C]/1 mL; PARATHYROID HORMONE 9 [hp_C]/1 mL; PYRIDOXINE HYDROCHLORIDE 12 [hp_C]/1 mL
INACTIVE INGREDIENTS: WATER; ALCOHOL

DRUG FACTS:

ACTIVE INGREDIENTS:

Berberis Vulgaris 6X, 9X, 12X, Calcarea Fluorica 12X 30C, Calcarea Phosphorica 6C, 9C, 30C, Calcarea Silicata 12X 30C, Chimaphila Umbellata 9X, 30C, Oxalicum Acidum 6X, 9X, 12X, 30C, Parathormonum 9C, Pyridoxinum Hydrochloricum 12C, Sanguinaria Canadensis 9X, Uricum Acidum 12X, 30C.

PURPOSE:

Berberis Vulgaris – Temporary relief of joint pain, Calcarea Fluorica - Temporary relief of bone pain, Calcarea Phosphorica - Temporary relief of back weakness, Calcarea Silicata - Temporary relief of skin itching, Chimaphila Umbellata - Temporary relief of urinary pain, Oxalicum Acidum - Temporary relief of back pain, Parathormonum – Parathyroid support, Pyridoxinum Hydrochloricum – Energy regulation, Sanguinaria Canadensis - Temporary relief of headaches, Uricum Acidum - Temporary relief of skin itching

USES:

Homeopathic remedy that regulates oxalate in the body.

*These "uses" have not been evaluated by the Food and Drug Administration.

**C, K, CK, and X are homeopathic dilutions see www.hpus.com

WARNINGS:

As with any drug, ask a doctor before use if pregnant or nursing.

Consult a physician if: Symptoms persist for more than 7 days or worsen.

Keep this and all medications out of the reach of children.

In case of accidental overdose, contact a medical professional or poison control center immediately.

Do not use if seal is broken or missing.

This Product does not contain sugar, starch, preservatives, artificial flavors or additives, and no wheat, gluten, soy, or milk derivatives.

KEEP OUT OF REACH OF CHILDREN:

In case of accidental overdose, contact a medical professional or poison control center immediately.

DIRECTIONS:

Adults and children 12 years of age and older: Take 1 full eyedropper twice a day to help alleviate symptoms of neurological disorders.

Under 12 years of age: Consult a physician.

INACTIVE INGREDIENTS

20% organic ethanol, purified water

QUESTIONS:

Distributed By:

Nucleic Products, LLC

PO Box 7148 Grove, OK 74344

Call weekdays 9am-5pm (918)791-1727

PACKAGE LABEL DISPLAY:

NDC: 75053-0012-1

Nu cleic

Oxaltem

Homeopathic Medicine

For Professional Use Only

4 fl oz. (118 ml)